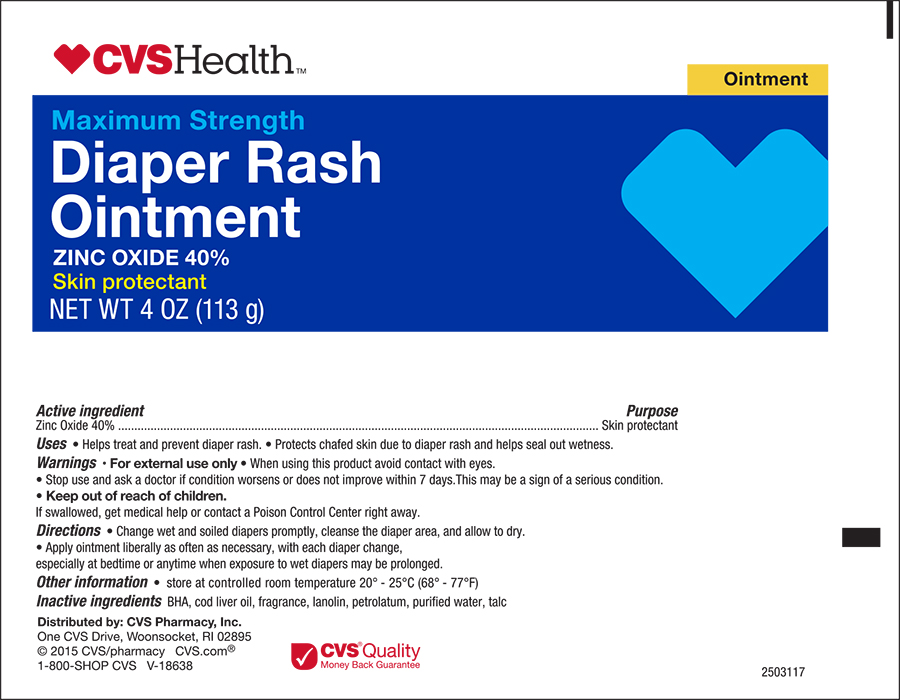 DRUG LABEL: CVS Health Diaper Rash
NDC: 69842-058 | Form: OINTMENT
Manufacturer: CVS Health
Category: otc | Type: HUMAN OTC DRUG LABEL
Date: 20170320

ACTIVE INGREDIENTS: ZINC OXIDE 400 mg/1 g
INACTIVE INGREDIENTS: BUTYLATED HYDROXYANISOLE; COD LIVER OIL; LANOLIN; PETROLATUM; TALC; WATER

CVS Diaper Rash Ointment

Drug Fact

Active Ingredient

Zinc Oxide 40%

Purpose

Skin protectant

Uses

- helps treat and prevent diaper rash
- protects chafed skin due to diaper rash and helps seal out wetness

Warnings

When using this product

- avoid contact with eyes

Stop use and ask a doctor if

- if condition worsens or does not improve in 7 days. This may be a sign of a seriuos condition.

Keep out of reach of children.

If swallowed, get medical help or contact a Poison Control Center right away.

Directions

- change wet and soiled diapers promptly
- cleanse the diaper area, and allow to dry
- apply ointment liberally as often as necessary, with each diaper change, especially at bedtime or anytime when exposure to wet diapers may be prolonged

Other information

store at room temperature 20° - 25°C (68° - 77°F)

Inactive ingredients

BHA, Cod liver oil, Fragrance, Lanolin, Petrolatum, Talc, Water

Principal Display Panel - Tube /Carton Label

CVS Health Compare to the Active Ingredients in Desitin

Maximuim Strength

Diaper Rash Ointment

ZINC OXIDE 40%

Skin protectant

NET WT 4 oz (113g)